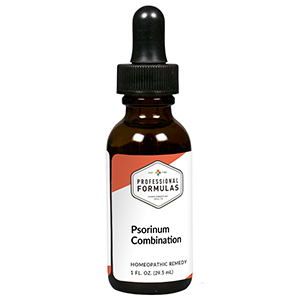 DRUG LABEL: Psorinum Combination
NDC: 63083-9237 | Form: LIQUID
Manufacturer: Professional Complementary Health Formulas
Category: homeopathic | Type: HUMAN OTC DRUG LABEL
Date: 20190815

ACTIVE INGREDIENTS: NERIUM OLEANDER WHOLE 4 [hp_X]/29.5 mL; CICUTA VIROSA WHOLE 5 [hp_X]/29.5 mL; SULFUR 6 [hp_X]/29.5 mL; THUJA OCCIDENTALIS LEAF 6 [hp_X]/29.5 mL; GONORRHEAL URETHRAL SECRETION HUMAN 12 [hp_X]/29.5 mL; SODIUM CHLORIDE 12 [hp_X]/29.5 mL; SCABIES LESION LYSATE (HUMAN) 12 [hp_X]/29.5 mL; TREPONEMIC SKIN CANKER HUMAN 12 [hp_X]/29.5 mL; BOVINE TUBERCULIN 12 [hp_X]/29.5 mL; VACCINIA VIRUS STRAIN NEW YORK CITY BOARD OF HEALTH LIVE ANTIGEN 12 [hp_X]/29.5 mL
INACTIVE INGREDIENTS: ALCOHOL; WATER

R237

ACTIVE INGREDIENTS

Oleander 4X
Cicuta virosa 5X
Sulphur 6X
Thuja occidentalis 6X
Medorrhinum 12X
Natrum muriaticum 12X
Psorinum 12X
Syphilinum 12X
Tuberculinum 12X
Vaccinotoxinum 12X

QUESTIONS

Professional Formulas

PO Box 2034 Lake Oswego, OR 97035

INDICATIONS

For the temporary relief of dry, irritated, red, or itchy skin.*

PURPOSE

*Claims based on traditional homeopathic practice, not accepted medical evidence. Not FDA evaluated.

WARNINGS

Consult a doctor if condition worsens or if symptoms persist. Keep out of the reach of children. In case of overdose, get medical help or contact a poison control center right away. If pregnant or breastfeeding, ask a healthcare professional before use.

Keep out of the reach of children.

PREGNANCY OR BREAST FEEDING

If pregnant or breastfeeding, ask a healthcare professional before use.

DIRECTIONS

Place drops under tongue 30 minutes before/after meals. Adults and children 12 years and over: Take 10 drops up to 3 times per day. Consult a physician for use in children under 12 years of age.

OTHER INFORMATION

Tamper resistant. If seal is broken, do not use. After opening, close container tightly and store at room temperature away from heat.

INACTIVE INGREDIENTS

40% ethanol, purified water.

LABEL

Est 1985

Professional Formulas

Complementary Health

Psorinum Combination

Homeopathic Remedy

1 FL. OZ. (29.5 mL)